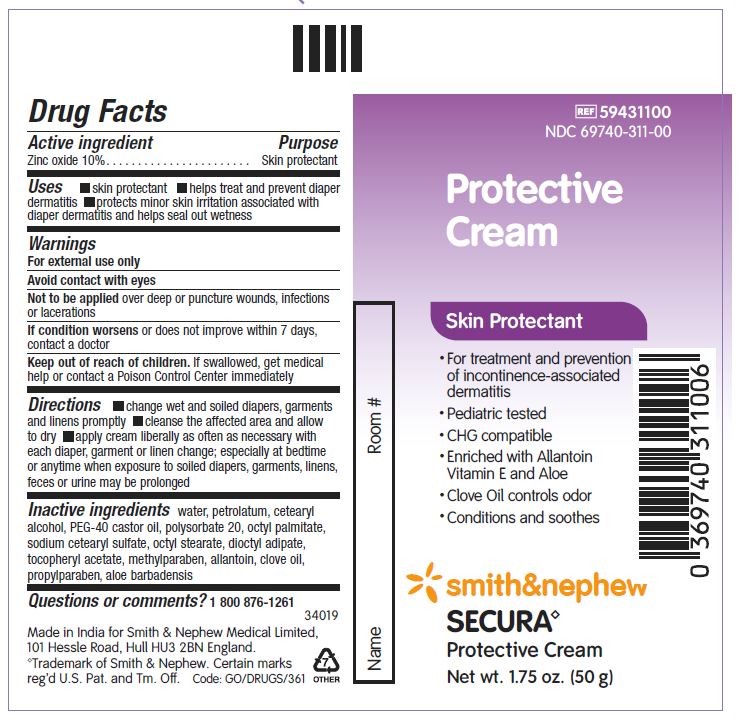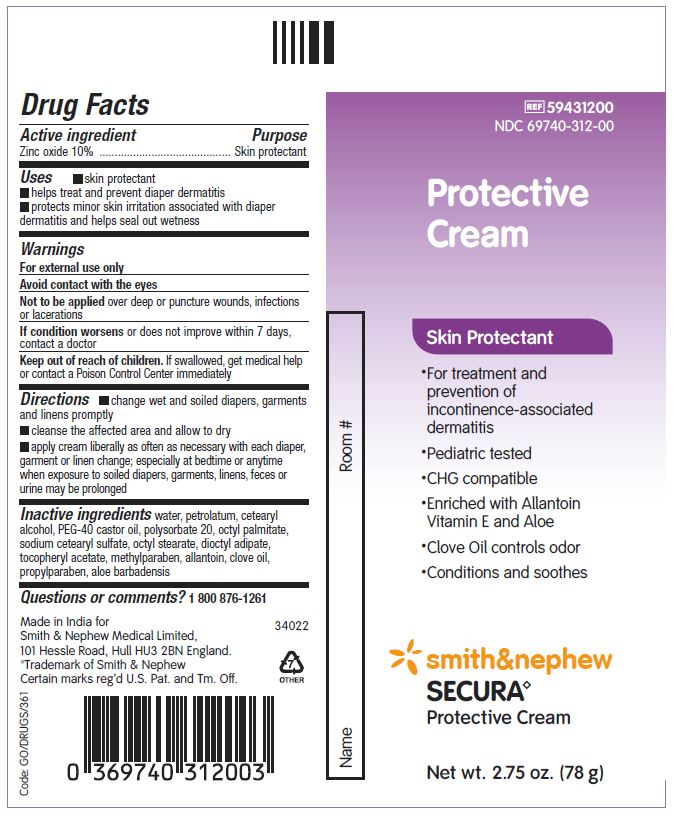 DRUG LABEL: Secura Protective
NDC: 69740-312 | Form: CREAM
Manufacturer: Smith & Nephew Medical Ltd
Category: otc | Type: HUMAN OTC DRUG LABEL
Date: 20240612

ACTIVE INGREDIENTS: ZINC OXIDE 100 mg/1 g
INACTIVE INGREDIENTS: ALOE VERA LEAF; PROPYLPARABEN; POLYSORBATE 20; OCTYL STEARATE; WATER; ALLANTOIN; CLOVE OIL; METHYLPARABEN; SODIUM CETOSTEARYL SULFATE; ALPHA-TOCOPHEROL ACETATE; PETROLATUM; CETOSTEARYL ALCOHOL; POLYOXYL 40 CASTOR OIL; OCTYL PALMITATE; DIOCTYL ADIPATE

Secura Protective Cream

ACTIVE INGREDIENT

Zinc oxide 10%

PURPOSE

Skin protectant

USES

- skin protectant
- helps treat and prevent diaper dermatitis
- protects minor skin irritation associated with diaper dermatitis and helps seal out wetness

WARNINGS

- For external use only
- Avoid contact with eyes
- Not to be applied over deep or puncture wounds, infections or lacerations
- If condition worsens or does not improve within 7 days, contact a doctor
- Keep out of reach of children. If swallowed, get medical help or contact a Poison Control Center immediately

WHEN USING

- Avoid contact with eyes

DO NOT USE

- Not to be appliedover deep or puncture wounds, infections or lacerations

STOP USE

- If condition worsensor does not improve within 7 days, contact a doctor

- Keep out of reach of children.If swallowed, get medical help or contact a Poison Control Center immediately

DIRECTIONS

- change wet and soiled diapers, garments, and linens promptly
- cleanse the affected area and allow to dry
- apply cream liberally as often as necessary with each diaper, garment or linen change; especially at bedtime or anytime when exposure to soiled diapers, garments, linens, feces, or urine may be prolonged

INACTIVE INGREDIENTS

water, petrolatum, cetearyl alcohol, PEG-40 castor oil, polysorbate 20, octyl palmitate, sodium cetearyl sulfate, octyl stearate, dioctyl adipate, tocopheryl acetate, methylparaben, allantoin, clove oil, propylparaben, aloe barbadensis

QUESTION OR COMMENTS?

1 800 876-1261

PACKAGE LABEL - PRINCIPAL DISPLAY PANEL- TUBE (50g)

REF 59431100

NDC69740-311-00

Protective Cream

Skin Protectant

- For treatment and prevention of incontinence-asssociated dermatitis
- Pediatric tested
- CHG compatible
- Enriched with Allantoin, Vitamin E and Aloe
- Clove Oil controls odor
- Conditions and soothes

Smith & Nephew

Secura◊

Protective Cream

Made in India for:
Smith & Nephew Medical Ltd, 101 Hessle Road
Hull, HU3 2BN, England

www.smith-nephew.com

◊Trademark of Smith & Nephew

Certain markes reg’d US Pat. And Tm Off.

PACKAGE LABEL - PRINCIPAL DISPLAY PANEL- TUBE (78g)

REF 59431200

NDC69740-312-00

Protective Cream

Skin Protectant

- For treatment and prevention of incontinence-asssociated dermatitis
- Pediatric tested
- CHG compatible
- Enriched with Allantoin, Vitamin E and Aloe
- Clove Oil controls odor
- Conditions and soothes

Smith & Nephew

Secura◊

Protective Cream

Made in India for:
Smith & Nephew Medical Ltd, 101 Hessle Road
Hull, HU3 2BN, England

www.smith-nephew.com

◊Trademark of Smith & Nephew

Certain markes reg’d US Pat. And Tm Off.